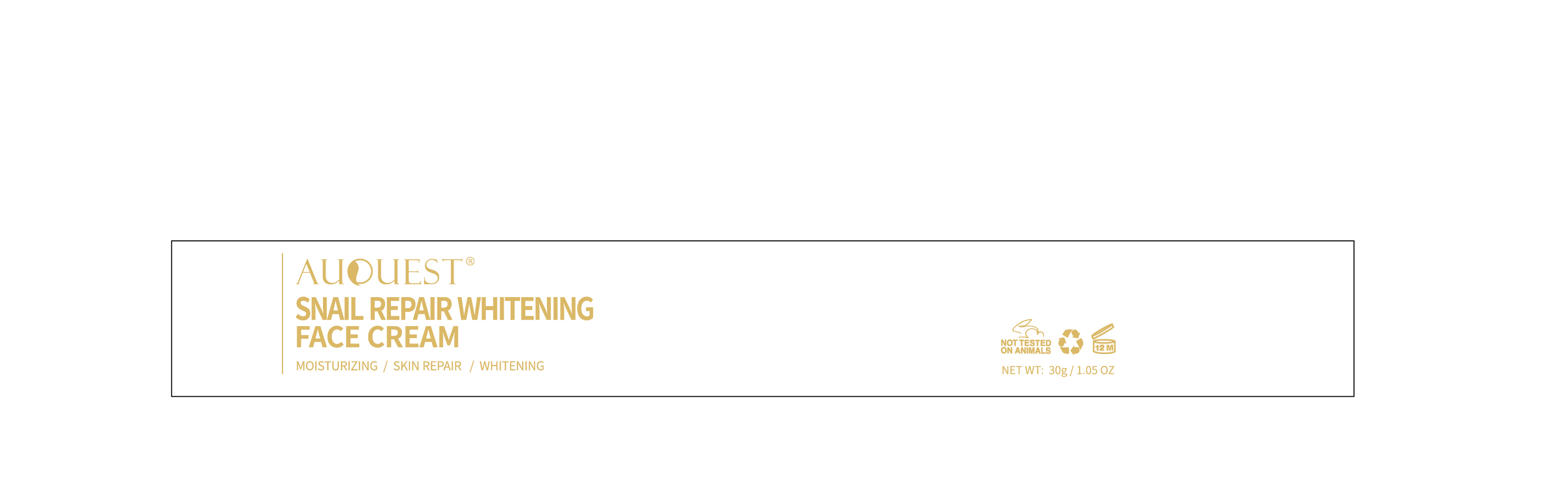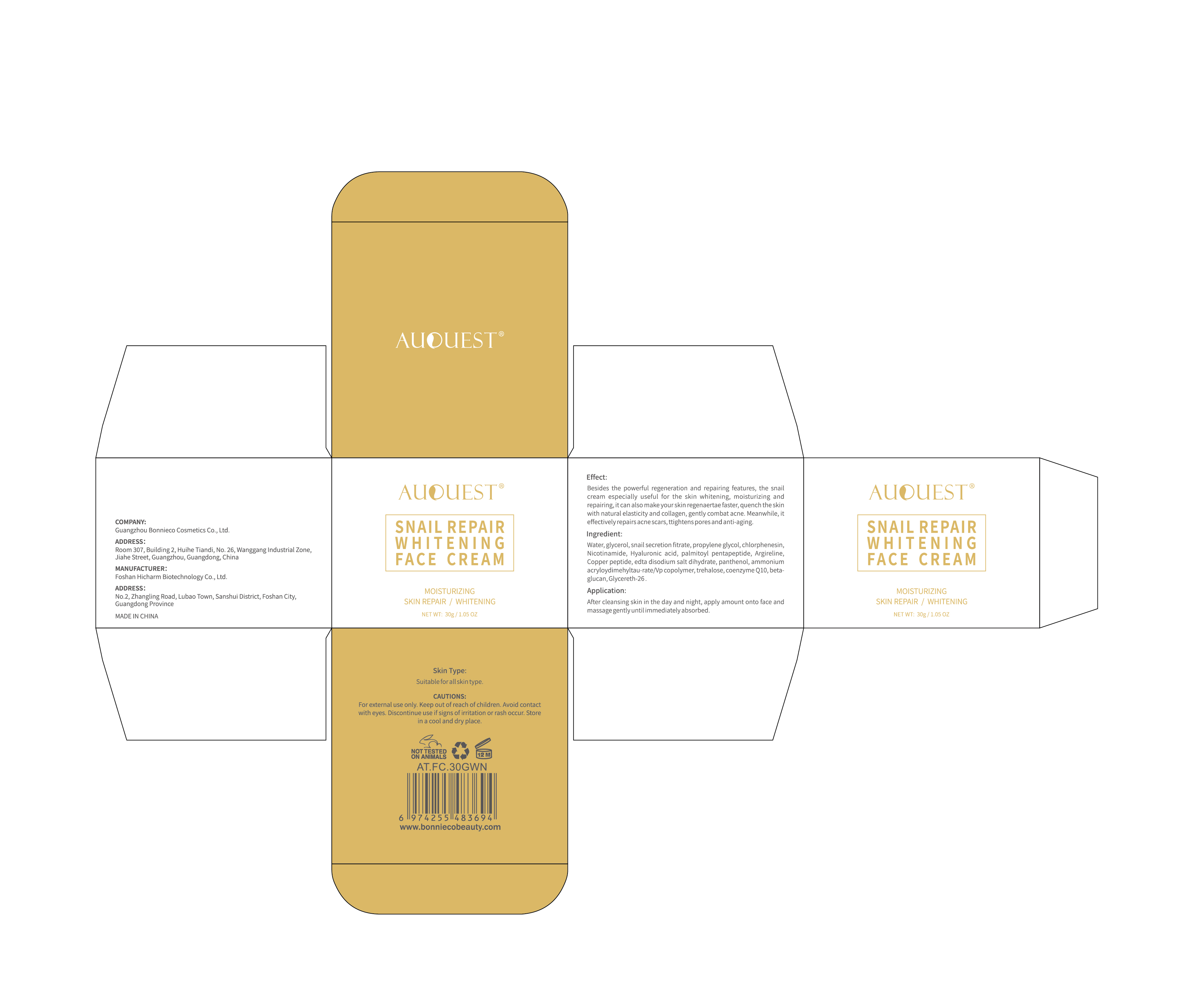 DRUG LABEL: Auquest Snail Repair Whitening Face Cream
NDC: 84186-013 | Form: CREAM
Manufacturer: Guangzhou Bonnieco Cosmetics Co., Ltd
Category: otc | Type: HUMAN OTC DRUG LABEL
Date: 20240409

ACTIVE INGREDIENTS: GLYCERIN 8 g/100 g
INACTIVE INGREDIENTS: PREZATIDE COPPER; CHLORPHENESIN; PROPYLENE GLYCOL; NIACINAMIDE; HYALURONIC ACID; SNAIL, UNSPECIFIED; ACETYL HEXAPEPTIDE-8; AMMONIUM CATION; TREHALOSE; TRANSFORMING GROWTH FACTOR BETA RECEPTOR TYPE 3; GLYCERETH-26; PANTHENOL; WATER; PALMITOYL PENTAPEPTIDE-4; EDETATE DISODIUM; UBIDECARENONE

84186-013

Active Ingredient

Glycerol 8%

Purpose

face (body part)

Use

After cleansing skin in the day and night, apply amount onto face andmassage gentlyuntilimmediately absorbed.

Warnings

For external use only. Keep out of reach of children.Avoid contactwith eyes. Discontinue use if signs of irritation or rash occur. Store，in a cool and dry place.

Do not use

Besides the powerful regeneration and repairing features, the snailcream especially useful for the skin whitening, moisturizing andrepairing,it can also make yourskin regenaertae faster, quench the skinwith natural elasticity and collagen, gently combat acne.Meanwhile, iteffectively repairs acne scars, ttightens pores and anti-aging.

When Using

In case of contact with the eyes, rinse immediately with plenty of water.

Stop Use

If discomfort arises, please immediately stop using the product and seek the assistance of a dermatologist.

Ask Doctor

If discomfort arises, please immediately stop using the product and seek the assistance of a dermatologist.

Keep Oot Of Reach Of Children

Directions

After cleansing skin in the day and night, apply amount onto face andmassage gentlyuntilimmediately absorbed.

Inactive ingredients

Water, snail secretion fitrate, propylene glycol, chlorphenesin,Nicotinamide，Hyaluronic acid,palmitoyl pentapeptide,Argireline,Copper peptide, edta disodium salt dihydrate, panthenol, ammoniumacryloydimehyltau-rate/Vp copolymer, trehalose, coenzyme Q10, beta-glucan,Glycereth-26.